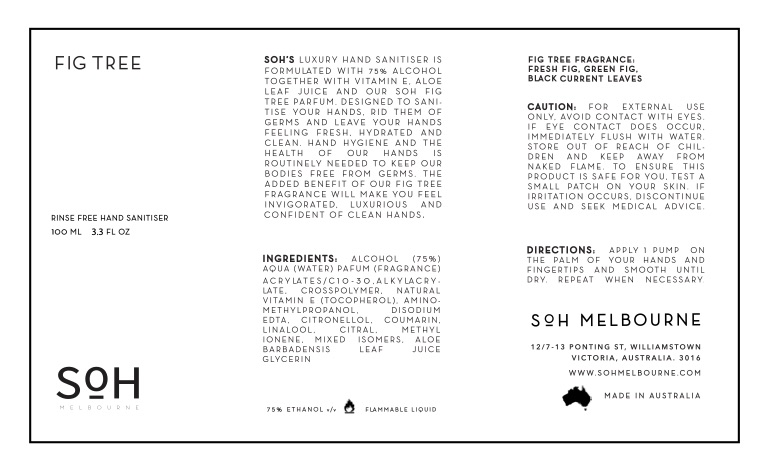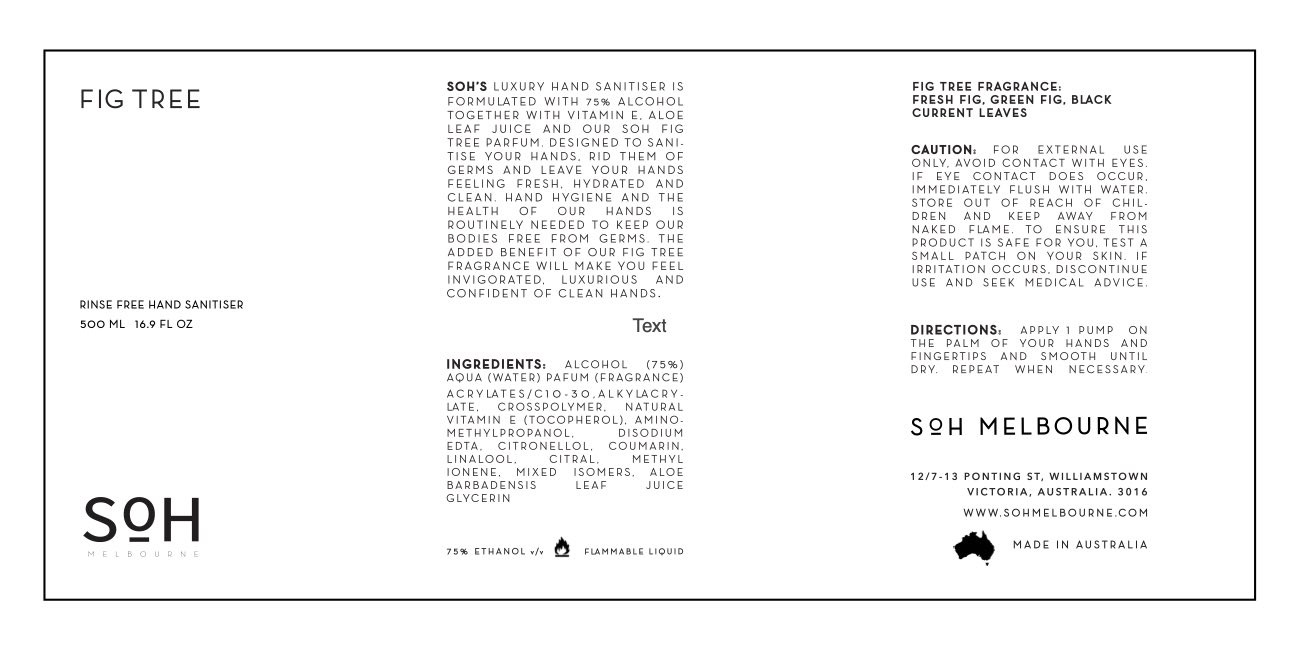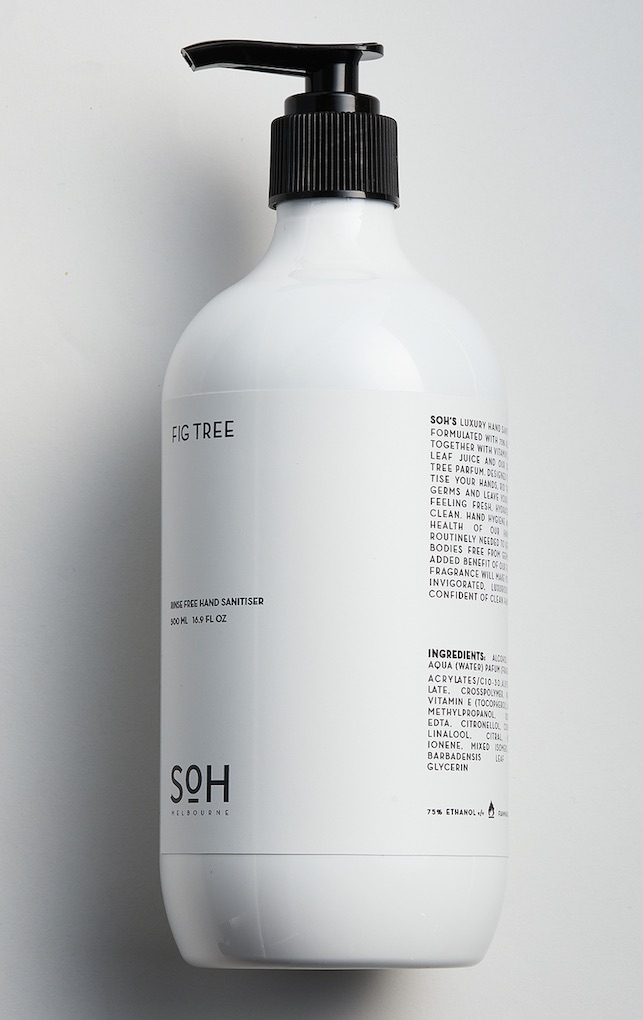 DRUG LABEL: SOH Hand Sanitizer
NDC: 78353-726 | Form: LIQUID
Manufacturer: The Scent of Home Pty Ltd
Category: otc | Type: HUMAN OTC DRUG LABEL
Date: 20200525

ACTIVE INGREDIENTS: ALCOHOL 75 mL/100 mL
INACTIVE INGREDIENTS: CARBOMER INTERPOLYMER TYPE A (ALLYL SUCROSE CROSSLINKED); GLYCERIN; WATER; ALOE VERA LEAF; TOCOPHEROL; AMINOMETHYLPROPANOL; EDETATE DISODIUM ANHYDROUS

Hand Sanitiser - Fig Tree

SOH Fig Tree Hand Sanitiser

This luxury hand sanitiser is formulated with 75% alcohol together with Vitamin E, Aloe Leaf Juice and our Fig Tree parfum. Created to sanitise your hands, rid them of germs and leave your hands feeling fresh, hydrated and clean.

Hand hygiene and the health of our hands is routinely needed to keep our bodies free from germs. The added benefit of our Fig Tree fragrance will make you feel invigorated and luxurious and confident of clean hands. The added element of Vitamin E and Aloe Barbadenis juice will keep your hands soft and moisturised.

Apply 1 pump on the palm of your hands. Massage into the back of your hands fingertips until dry. Repeat when necessary.

For external use only. Avoid contact with eyes.If eye contact occurs immediately flush with water. To ensure skin compatibility test product on a small patch of skin. Store out of reach of Children,

If skin irritation occurs discontinue and seek medical advice. Do not use on extremely damaged skin. Contains 75% Alcohol v/v. Made in Australia

Ingredients: Alcohol (75%), aqua (water), parfum (fragrance), acrylates/C10-30, alkylacrylate, crosspolymer, natural vitamin E (tocopherol), aminomethylpropanol, coumarin, linalool, citral, methyl ionene, mixed isomers, aloe barbadensis leaf juice, glycerin.

Active Ingredient(s)

Alcohol 80% v/v. Purpose: Antiseptic

Purpose

Antiseptic, Hand Sanitizer

Use

Hand Sanitizer to help reduce bacteria that potentially can cause disease. For use when soap and water are not available.

Warnings

For external use only. Flammable. Keep away from heat or flame

Do not use

- in children less than 2 months of age
- on open skin wounds

When using this product keep out of eyes, ears, and mouth. In case of contact with eyes, rinse eyes thoroughly with water.
Stop use and ask a doctor if irritation or rash occurs. These may be signs of a serious condition.
Keep out of reach of children. If swallowed, get medical help or contact a Poison Control Center right away.

Stop use and ask a doctor if irritation or rash occurs. These may be signs of a serious condition.

Keep out of reach of children. If swallowed, get medical help or contact a Poison Control Center right away.

Directions

- Place enough product on hands to cover all surfaces. Rub hands together until dry.
- Supervise children under 6 years of age when using this product to avoid swallowing.

Other information

- Store between 15-30C (59-86F)
- Avoid freezing and excessive heat above 40C (104F)

Inactive ingredients

aqua (water), parfum (fragrance), acrylates/C10-30 alkyl acrylate crosspolymer, natural vitamin E (tocopherol), aminomethylpropanol, coumarin, linalool, citral, methyl ionene, mixed isomers, aloe barbadensis leaf juice, glycerin.

500ml Hand Sanitiser

500ml NDC:78353-726-35

100ml Hand Sanitiser

100ml NDC: 78353-726-34